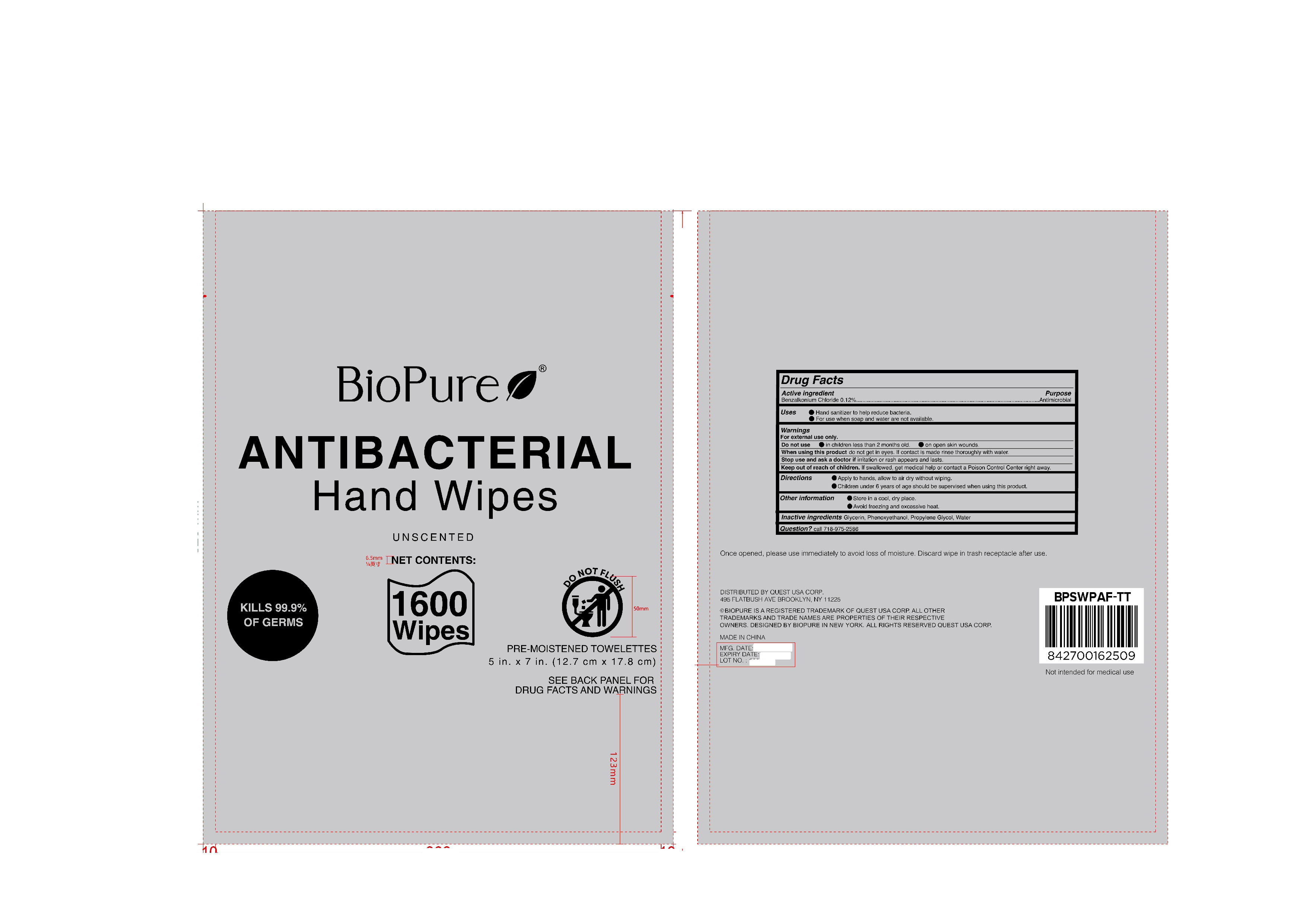 DRUG LABEL: BIOPURE 1600CT ANTIBACTERIAL HAND WIPES
NDC: 79794-112 | Form: PATCH
Manufacturer: Zhejiang Furuisen Spunlaced Nonwovens Co., Ltd.
Category: otc | Type: HUMAN OTC DRUG LABEL
Date: 20240719

ACTIVE INGREDIENTS: BENZALKONIUM CHLORIDE 0.12 g/100 g
INACTIVE INGREDIENTS: PROPYLENE GLYCOL; PHENOXYETHANOL; WATER; GLYCERIN

79794-112

Active ingredient

0.12% Benzalkonium Chloride

Purpose

Antibacterial

Uses

●Hand sanitizer to help reduce bacteria.

●For use when soap and water are not available

Warnings

For external use only.

Do not use

●in children less than 2 months old.

●on open skin wounds.

When using this product

do not get in eyes. If contact is made rinse thoroughly with water.

Stop use and ask a doctor if

irritation or rash appears and lasts.

Keep out of reach of children.

If swallowed, get medical help or contact a Poison Control Center right away.

Directions

●Apply to hands, allow to air dry without wiping.

●Children under 6 years of age should be supervised when using this product.

Other information

●Store in a cool, dry place.

●Avoid freezing and excessive heat .

Inactive ingredients

Glycerin, Phenoxyethanol, Propylene Glycol, Water

Question?

Call 718-975-2586